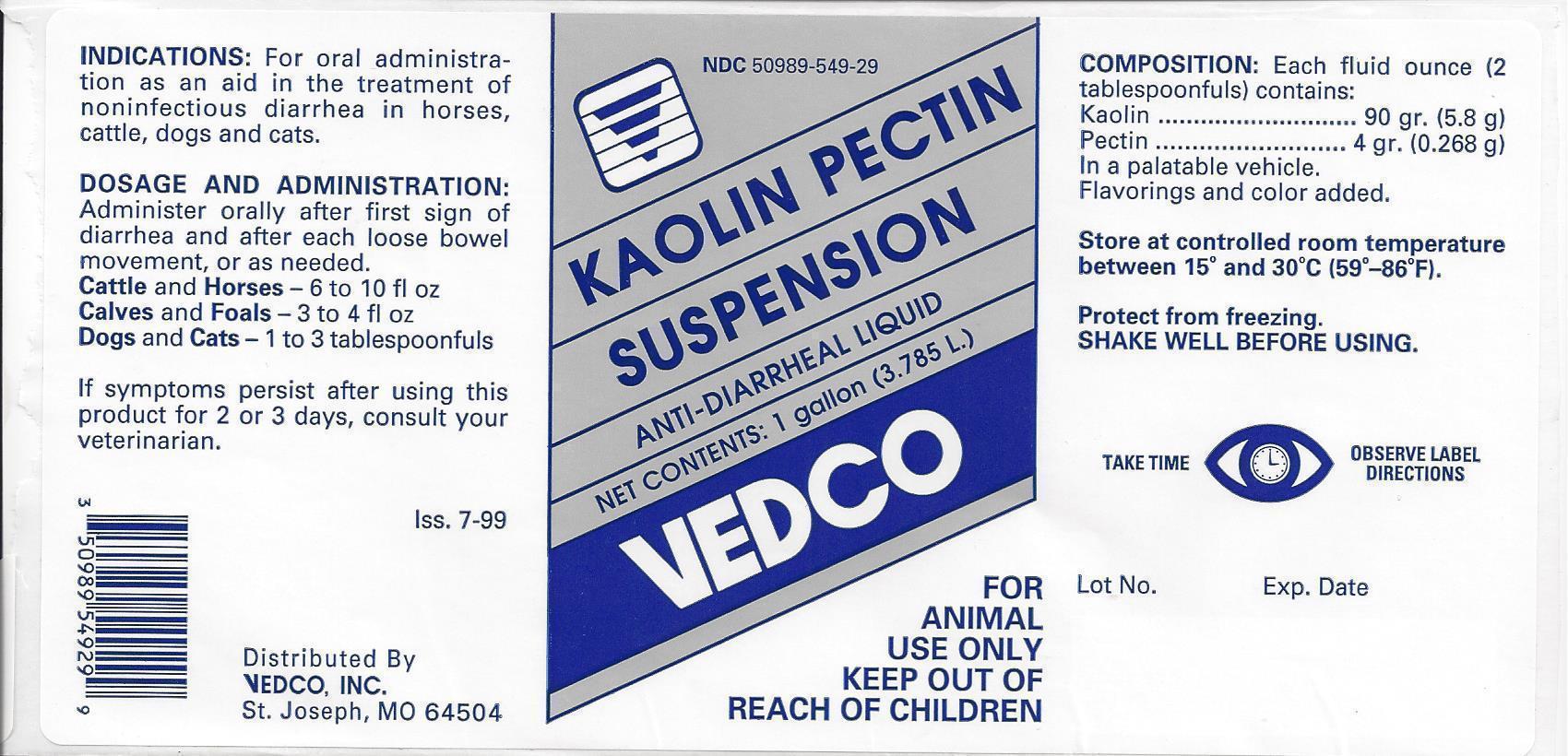 DRUG LABEL: Kaolin Pectin Suspension
NDC: 50989-549 | Form: SUSPENSION
Manufacturer: Vedco
Category: animal | Type: OTC ANIMAL DRUG LABEL
Date: 20130919

ACTIVE INGREDIENTS: KAOLIN 196 mg/1 mL; PECTIN, CITRUS 9 mg/1 mL
INACTIVE INGREDIENTS: GUAR GUM; METHYLPARABEN; POTASSIUM SORBATE; SACCHARIN SODIUM; PROPYLPARABEN; FD&C RED NO. 40; WATER

Kaolin Pectin Suspension

NDC 50989-549-29 KAOLIN PECTIN SUSPENSION ANTI-DIARRHEAL LIQUID NET CONTENTS: 1 gallon (3.785L)

VEDCO

FOR ANIMAL USE ONLY

KEEP OUT OF REACH OF CHILDREN

INDICATIONS:

For oral administration as an aid in the treatment of noninfectious diarrhea in horses, cattle, dogs and cats.

DOSAGE AND ADMINISTRATION:

Administer orally after first sign of diarrhea and after each loose bowel movement, or as needed.

Cattle and Horses: 6 to 10 fl oz

Calves and Foals: 3 to 4 fl oz

Dogs and Cats: 1 to 3 tablespoonfuls

If symptoms persist after using this product for 2 or 3 days, consult a veterinarian.

Iss. 7-99

Distributed By

VEDCO, INC.

St. Joseph, MO 64504

COMPOSITION:

Each fluid ounce (2 tablespoonfuls) contains:

Kaolin ... 90 gr. (5.8 g)

Pectin ..... 4 gr. (0.268 g)

In a palatable vehicle.

Flavorings and color added.

STORAGE AND HANDLING

Store at controlled room temperature between 15º and 30ºC (59º - 86ºF).

Protect from freezing.

SHAKE WELL BEFORE USING.

TAKE TIME OBSERVE LABEL DIRECTIONS

Lot No. Exp. Date